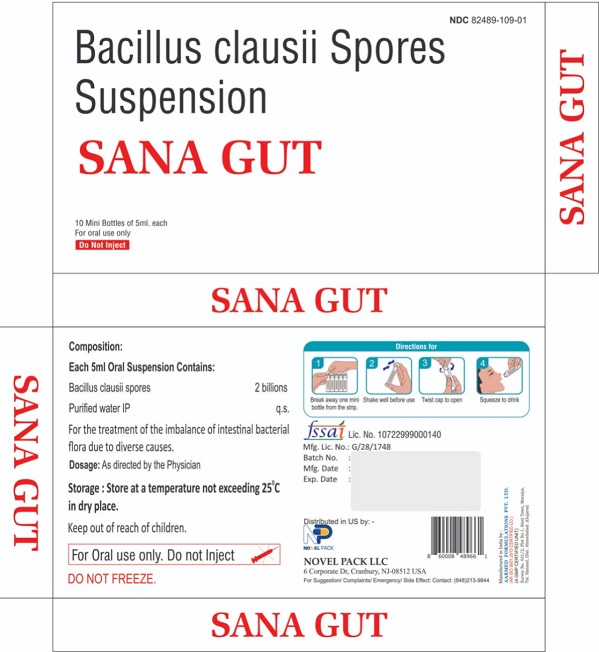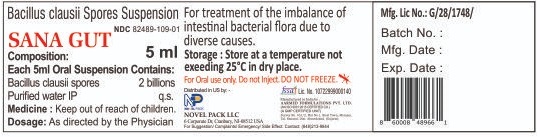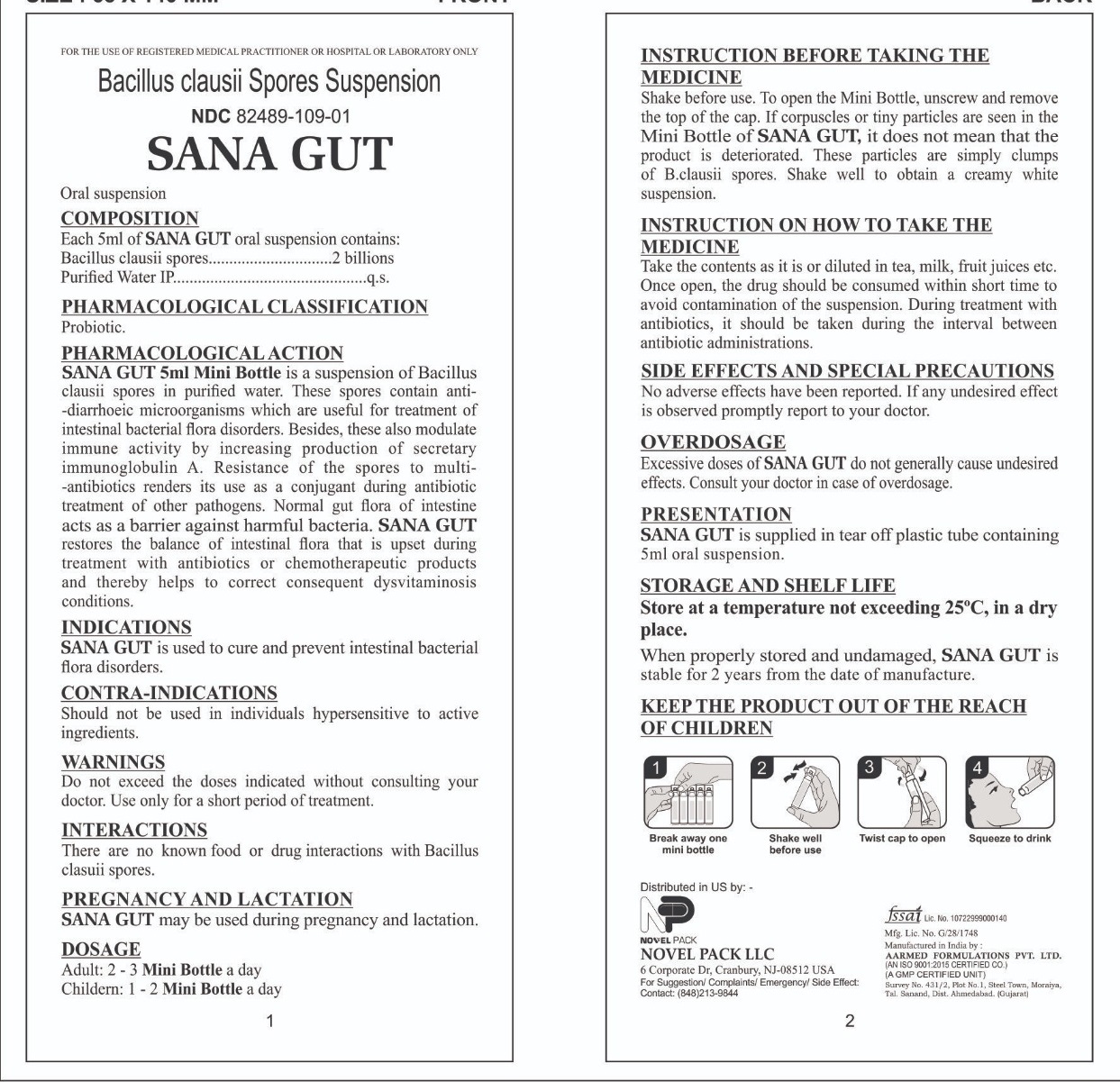 DRUG LABEL: SANA GUT
NDC: 82489-109 | Form: SUSPENSION
Manufacturer: NOVEL PACK LLC
Category: other | Type: DIETARY SUPPLEMENT
Date: 20220503

ACTIVE INGREDIENTS: BACILLUS CLAUSII 2000000000 1/1 1
INACTIVE INGREDIENTS: Water

SANA GUT
Bacillus Clausii Spores Suspension

STATEMENT OF IDENTITY

SANA GUT

Bacillus Clausii Spores

Suspension

Helps to balance intestinal bacterial flora due to diverse causes.

Storage Condition

Store at a temperature not exceeding 25 °C in dry place

Dosage

As directed by the physician.

PRECAUTIONS

INSTRUCTION BEFORE TAKING THE MEDICINE

Shake before use. To open the Mini Bottle, unscrew and remove the top of the cap. If corpuscles or tiny particles are seen in the Mini Bottle of SANA GUT, it does not mean tha the product is deteriorated. These particles are simply clumps of B.clausii spores. Shake well to obtain a cream white suspension.

INSTRUCTION ON HOW TO TAKE THE MEDICINE

Take the contents as it is or dilued in tea, milk, fruit juices etc. Once open, the drug should be consumed within short time to avoid contamination of the suspension. During treatment with antibiotics, it should be taken uring the interval between antibiotic administraiton.